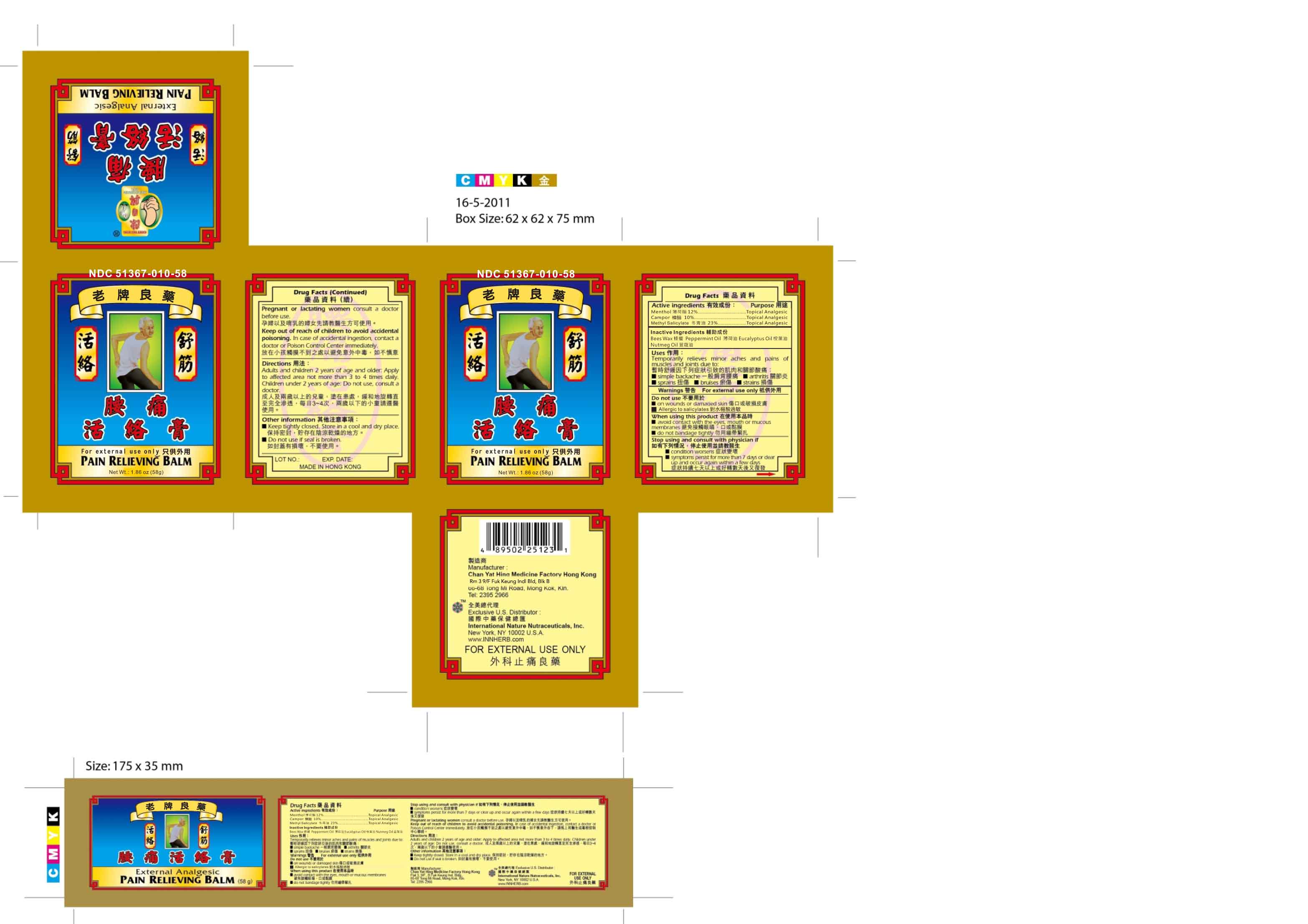 DRUG LABEL: Pain Relieving Balm
NDC: 51367-010 | Form: LINIMENT
Manufacturer: International Nature Nutraceuticals, Inc.
Category: otc | Type: HUMAN OTC DRUG LABEL
Date: 20130804

ACTIVE INGREDIENTS: MENTHOL 6.19 g/1 1; CAMPHOR (NATURAL) 5.78 g/1 1; METHYL SALICYLATE 15.66 g/1 1
INACTIVE INGREDIENTS: YELLOW WAX; PEPPERMINT OIL; EUCALYPTUS OIL; NUTMEG OIL

Drug Facts

Active Ingredients

Menthol- 12%

Camphor- 10%

Methyl Salicylate- 23%

Uses

Temporarily relieves minor aches and pains of muscles and joints due to:

- simple backache
- arthritis
- sprains
- bruises
- strains

Warnings

For External Use Only

Do Not Use

- on wounds or damaged skin
- if allergic to salicylates

When using this product

Avoid contact with the eyes, mouth, or mucous membranes

Do not bandage tightly

Stop using and consult with physician if

Condition worsens

Symptoms persist for more than 7 days or clear up and occur again within a few days

Safety

Pregnant or lactating women consult a doctor before use

In case of accidental ingestion contact a doctor or Poision control center immediately

Directions

Adults and children 2 years of age and older: apply to affected area not more than 3 to 4 times daily

Children under 2 years of age: Do not use, consult a doctor

Other Information

Keep tightly closed

Store in a cool and dry place

Do not use if seal is broken

Inactive Ingredients

Bees wax, Peppermint oil, Eucalyptus oil, Nutmeg oil